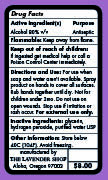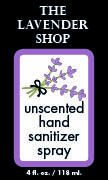 DRUG LABEL: Hand Sanitizer
NDC: 75554-417 | Form: AEROSOL, SPRAY
Manufacturer: The Lavender Shop
Category: otc | Type: HUMAN OTC DRUG LABEL
Date: 20200415

ACTIVE INGREDIENTS: ALCOHOL 80 mL/100 mL
INACTIVE INGREDIENTS: GLYCERIN 1.45 mL/100 mL; HYDROGEN PEROXIDE 0.125 mL/100 mL; WATER

Active Ingredient(s)

Alcohol 80% v/v. Purpose: Antiseptic

PURPOSE

Antiseptic

Flammable

Keep away from heat or flame

Keep out of reach of children.

If ingested get medical help or call a Poison Control Center immediately.

Directions and Use

For use when soap and water aren’t available. Spray product on hands to cover all surfaces. Rub hands together until dry. Not for children under 2mo. Do not use on open wounds. Stop use if irritation or rash occur. For external use only.

Directions

- Place enough product on hands to cover all surfaces. Rub hands together until dry.
- Supervise children under 6 years of age when using this product to avoid swallowing.

Inactive ingredients

glycerin, hydrogen peroxide, purified water USP

Other information

Store below 40C (104F). Avoid freezing.

Directions and Use

For use when soap and water aren’t available. Spray product on hands to cover all surfaces. Rub hands together until dry. Not for children under 2mo. Do not use on open wounds. Stop use if irritation or rash occur. For external use only.

Package Label - Principal Display Panel

118 mL NDC: 75554-417-20